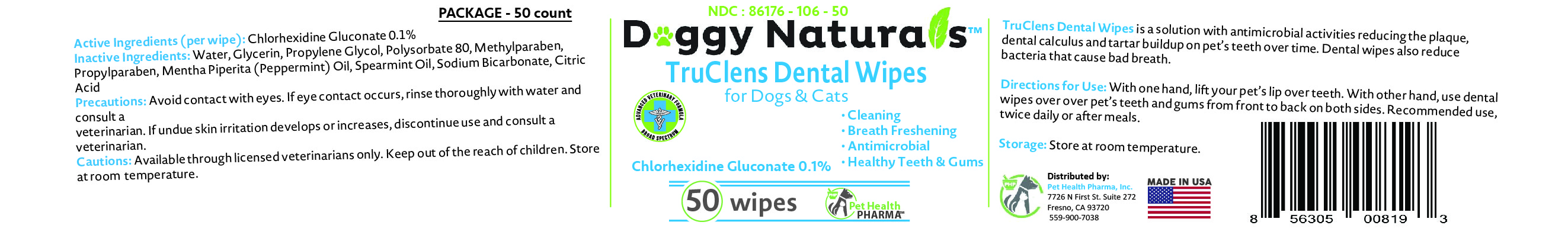 DRUG LABEL: TRUCLENS DENTAL WIPES FOR CATS AND DOGS
NDC: 86176-106 | Form: CLOTH
Manufacturer: Pet Health Pharma, LLC
Category: animal | Type: OTC ANIMAL DRUG LABEL
Date: 20210101

ACTIVE INGREDIENTS: CHLORHEXIDINE GLUCONATE 0.001 g/1 1
INACTIVE INGREDIENTS: WATER; GLYCERIN; PROPYLENE GLYCOL; POLYSORBATE 80; METHYLPARABEN; PROPYLPARABEN; PEPPERMINT OIL; SPEARMINT OIL; SODIUM BICARBONATE; CITRIC ACID MONOHYDRATE

TRUCLENS DENTAL WIPES FOR CATS AND DOGS

Active Ingredients (per wipe):

Chlorhexidine Gluconate 0.1%

PURPOSE:

Antimicrobial

Inactive Ingredients:

Water, Glycerin, Propylene Glycol, Polysorbate 80, Methylparaben, Propylparaben, Mentha Piperita (Peppermint) Oil, Spearmint Oil, Sodium Bicarbonate, Citric Acid

INDICATIONS & USAGE:

TruClens Dental Wipes is a solution with antimicrobial activities reducing the plaque, dental calculus and tartar buildup on pet’s teeth over time. Dental wipes also reduce bacteria that cause bad breath.

DOSAGE & ADMINISTRATION:

With one hand, lift your pet’s lip over teeth. With other hand, use dental wipes over pet’s teeth and gums from front to back on both sides. Recommended use, twice daily or after meals.

STORAGE AND HANDLING:

Store at room temperature

PRECAUTIONS:

Avoid contact with eyes. If eye contact occurs, rinse thoroughly with water and consult a veterinarian. If undue skin irritation develops or increases, discontinue use and consult a veterinarian.

Cautions

Keep out of the reach of children.

SPL UNCLASSIFIED SECTION

for Dogs & Cats

Made IN USA

- Cleaning
- Breath Freshening
- Antimicrobial
- Healthy Teeth & Gums

ADVANCED VETERINARY FORMULA

BROAD SPECTRUM

Distributed by:
Pet Health Pharma, Inc.
7726 N First St. Suite 272
Fresno, CA 93720
559-900-7038

Packaging

Add image transcription here...